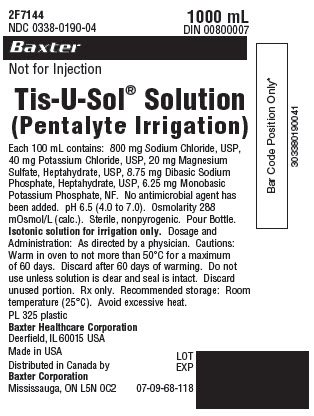 DRUG LABEL: TIS-U-SOL
NDC: 0338-0190 | Form: IRRIGANT
Manufacturer: Baxter Healthcare Corporation
Category: prescription | Type: HUMAN PRESCRIPTION DRUG LABEL
Date: 20140221

ACTIVE INGREDIENTS: SODIUM CHLORIDE 800 mg/100 mL; POTASSIUM CHLORIDE 40 mg/100 mL; MAGNESIUM SULFATE HEPTAHYDRATE 20 mg/100 mL; SODIUM PHOSPHATE, DIBASIC, HEPTAHYDRATE 8.75 mg/100 mL; MONOBASIC POTASSIUM PHOSPHATE 6.25 mg/100 mL
INACTIVE INGREDIENTS: WATER

DESCRIPTION

Tis-U-Sol® Solution

(Pentalyte Irrigation)

Each 100 mL contains: 800 mg Sodium Chloride, USP, 40 mg Potassium Chloride, USP, 20 mg Magnesium Sulfate, Heptahydrate, USP, 8.75 mg Dibasic Sodium Phosphate, Heptahydrate, USP, 6.25 mg Monobasic Potassium Phosphate, NF. No antimicrobial agent has been added. pH 6.5 (4.0 to 7.0). Osmolarity 288 mOsmol/L (calc.). Sterile, nonpyrogenic. Pour Bottle.

INDICATIONS AND USAGE

Isotonic solution for irrigation only. Not for injection.

DOSAGE AND ADMINISTRATION

As directed by a physician.

Cautions: Warm in oven to not more than 50°C for a maximum of 60 days. Discard after 60 days of warming. Do not use unless solution is clear and seal is intact. Discard unused portion. Rx only.

HOW SUPPLIED

Recommended storage: Room temperature (25°C). Avoid excessive heat.

PRINCIPAL DISPLAY PANEL - PACKAGING LABELING

2F7144
NDC 0338-0190-04

1000 mL
DIN 00800007

Baxter Logo
Not for Injection

Tis-U-Sol® Solution
(Pentalyte Irrigation)

Each 100 mL contains: 800 mg Sodium Chloride, USP,
40 mg Potassium Chloride, USP, 20 mg Magnesium
Sulfate, Heptahydrate, USP, 8.75 mg Dibasic Sodium
Phosphate, Heptahydrate, USP, 6.25 mg Monobasic
Potassium Phosphate, NF. No antimicrobial agent has
been added. pH 6.5 (4.0 to 7.0). Osmolarity 288
mOsmol/L (calc.). Sterile, nonpyrogenic. Pour Bottle.
Isotonic solution for irrigation only. Dosage and
Administration: As directed by a physician. Cautions:
Warm in oven to not more than 50°C for a maximum
of 60 days. Discard after 60 days of warming. Do not
use unless solution is clear and seal is intact. Discard
unused portion. Rx only. Recommended storage: Room
temperature (25°C). Avoid excessive heat.

PL 325 plastic

Baxter Healthcare Corporation
Deerfield, IL 60015 USA

Made in USA

Distributed in Canada by
Baxter Corporation
Mississauga, ON
L5N OC2

07-09-68-118

Bar Code Position Only*
303380190041

LOT
EXP